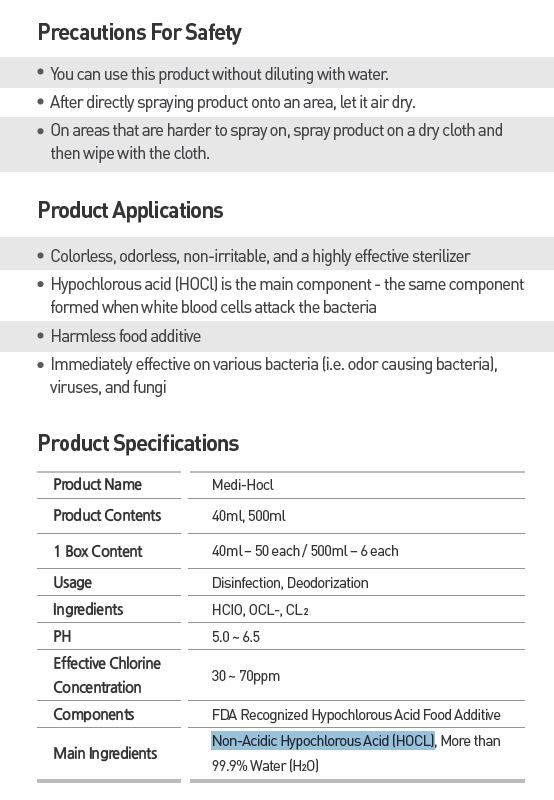 DRUG LABEL: CLAON HOCL
NDC: 70694-0001 | Form: LIQUID
Manufacturer: Inc MBG
Category: otc | Type: HUMAN OTC DRUG LABEL
Date: 20190124

ACTIVE INGREDIENTS: HYPOCHLOROUS ACID 1 g/100 mL
INACTIVE INGREDIENTS: WATER

INDICATIONS AND USAGE

spray proper amount to the product

Keep out of reach of children.

DOSAGE AND ADMINISTRATION

for external use only

WARNINGS

After directly spraying product onto an area, let it air dry.
On areas that are harder to spray on, spray product on a dry cloth and then wipe with the cloth.

PURPOSE

Immediately effective on various bacteria (i.e. odor causing bacteria), viruses, and fungi

INACTIVE INGREDIENT

water

ACTIVE INGREDIENT

Non-Acidic Hypochlorous Acid (HOCL)